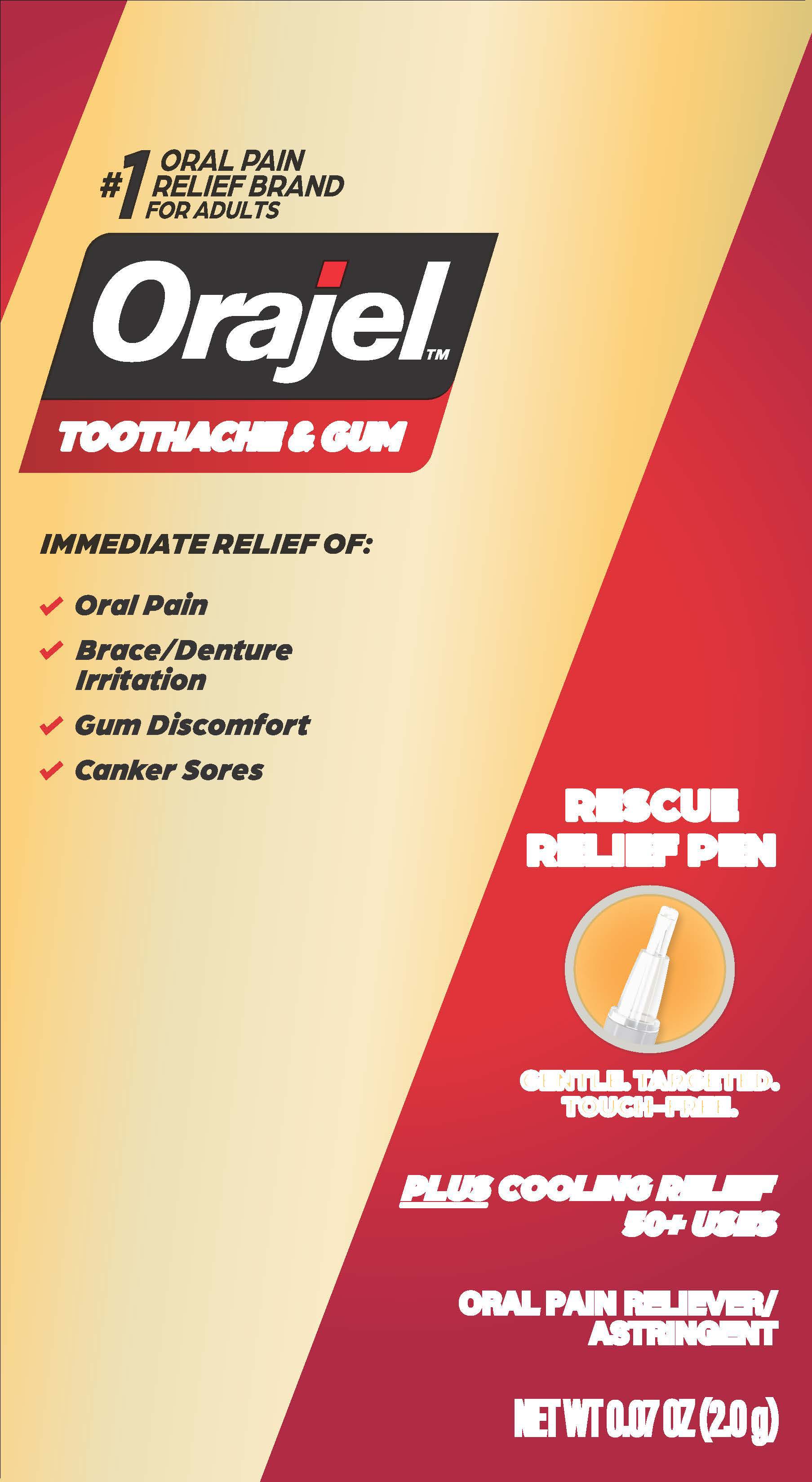 DRUG LABEL: Orajel Rescue Relief Pen
NDC: 10237-731 | Form: GEL
Manufacturer: Church & Dwight Co., Inc.
Category: otc | Type: HUMAN OTC DRUG LABEL
Date: 20250601

ACTIVE INGREDIENTS: ZINC CHLORIDE 1.5 mg/1 g; MENTHOL 2.6 mg/1 g; BENZOCAINE 200 mg/1 g
INACTIVE INGREDIENTS: AMMONIUM GLYCYRRHIZATE; WATER; SORBIC ACID; POLYETHYLENE GLYCOL 400; PEG-75; SODIUM SACCHARIN

Orajel Rescue Relief Pen

ACTIVE INGREDIENTS

Benzocaine 20%
Menthol 0.26%

Zinc chloride 0.15%

PURPOSE

Oral Pain Reliever / Oral Astringent

USES

• for the temporary relief of
• pain due to minor irritation or injury of the mouth and gums
• occasional sore mouth and sore throat

WARNINGS

Methemoglobinemia warning: Use of this product may cause methemoglobinemia, a serious condition that must be treated promptly because it reduces the amount of oxygen carried in blood. This can occur even if you have used this product before. Stop use and seek immediate medical attention if you or a child in your care develops:• pale, gray, or blue colored skin (cyanosis) • headache • rapid
heart rate • shortness of breath • dizziness or lightheadedness • fatigue or lack of energy

Allergy alert: do not use this product if you have a history of allergy to local anesthetics such as procaine, butacaine, benzocaine or other "caine" anesthetics

DO NOT USE

• more than directed

• for more than 7 days unless directed by a dentist or doctor

• for teething

• in children under 2 years of age

STOP USE AND ASK A DENTIST OR DOCTOR IF

• sore throat is severe, persists for more than 2 days

• sore mouth symptoms do not improve in 7 days

• headache, nausea, vomiting, swelling, rash or fever develops

• irritation, pain or redness persists or worsens

KEEP OUT OF REACH OF CHILDREN

In case of overdose or allergic reaction, get medical help or contact a Poison Control Center right away.

DIRECTIONS

adults and children 2 years of age and older | apply to the affected area up to 4 times daily or as directed by a dentist or doctor
children between 2 and 12 years of age | ask a doctor before use. Should be supervised in the use of this product.
children under 2 years of age | do not use

OTHER INFORMATION

• do not use if package has been opened

INACTIVE INGREDIENTS

ammonium glycrrhizate, flavor, PEG-8, PEG-75, sodium saccharin, sorbic acid, water

QUESTIONS OR COMMENTS?

Call us at 1-800-952-5080 M-F 9am-5pm ET or visit our website at www.orajel.com

PACKAGE LABEL

#1 ORAL PAIN

RELIEF BRAND

FOR ADULTS

Orajel™

TOOTHACHE & GUM

IMMEDIATE RELIEF OF:

ORAL PAIN

BRACE/DENTURE IRRITATION

GUM DISCOMFORT

CANKER SORES

RESCUE RELIEF PEN

GENTLE. TARGETED. TOUCH-FREE.

PLUS COOLING RELIEF

50+ USES

ORAL PAIN RELIEVER / ASTRINGENT

NET WT 0.07 OZ (2.0 g)